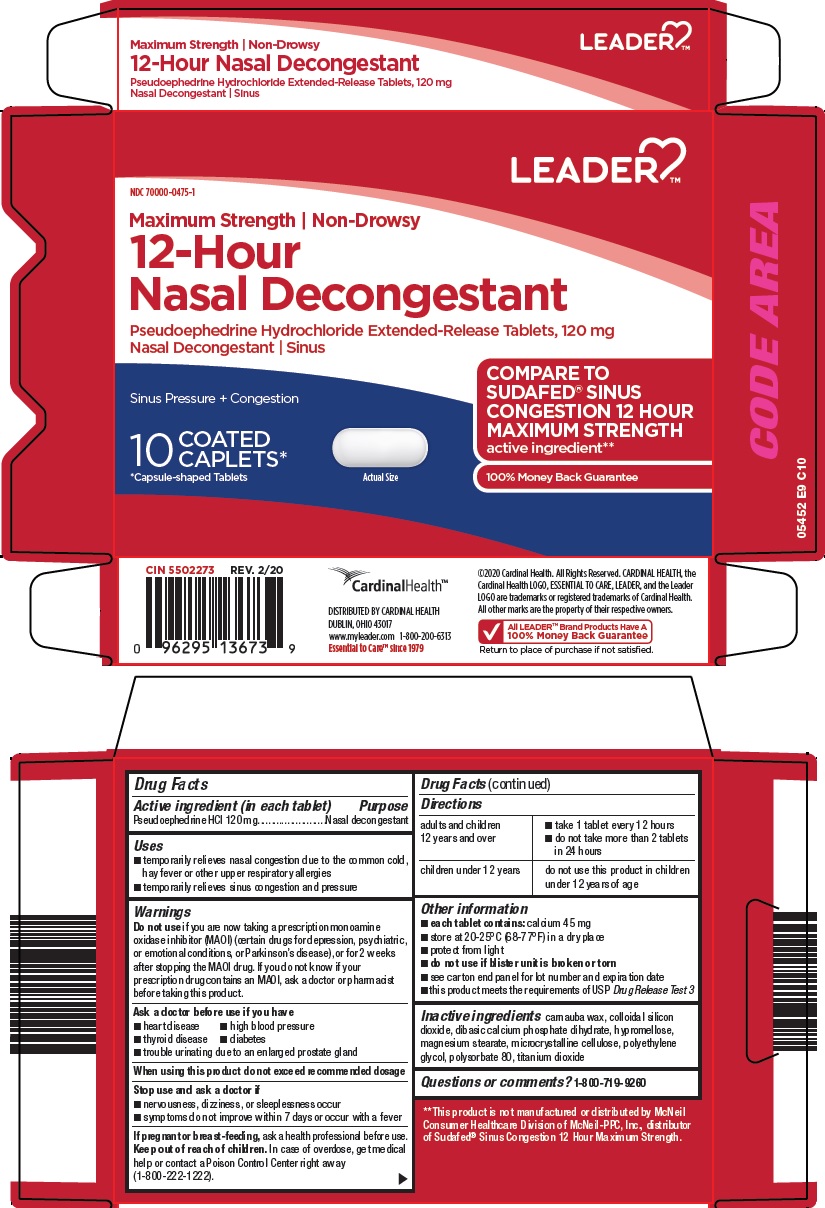 DRUG LABEL: leader 12 hour nasal decongestant
NDC: 70000-0475 | Form: TABLET, FILM COATED, EXTENDED RELEASE
Manufacturer: Cardinal Health 110, LLC. dba Leader
Category: otc | Type: HUMAN OTC DRUG LABEL
Date: 20260225

ACTIVE INGREDIENTS: PSEUDOEPHEDRINE HYDROCHLORIDE 120 mg/1 1
INACTIVE INGREDIENTS: CARNAUBA WAX; SILICON DIOXIDE; DIBASIC CALCIUM PHOSPHATE DIHYDRATE; HYPROMELLOSE, UNSPECIFIED; MAGNESIUM STEARATE; MICROCRYSTALLINE CELLULOSE; POLYETHYLENE GLYCOL, UNSPECIFIED; POLYSORBATE 80; TITANIUM DIOXIDE

Cardinal Health 12 Hour Nasal Decongestant Drug Facts

Active ingredient (in each tablet)

Pseudoephedrine HCl 120 mg

Purpose

Nasal decongestant

Uses

- temporarily relieves nasal congestion due to the common cold, hay fever or other upper respiratory allergies
- temporarily relieves sinus congestion and pressure

Warnings

Do not use

if you are now taking a prescription monoamine oxidase inhibitor (MAOI) (certain drugs for depression, psychiatric, or emotional conditions, or Parkinson’s disease), or for 2 weeks after stopping the MAOI drug. If you do not know if your prescription drug contains an MAOI, ask a doctor or pharmacist before taking this product.

Ask a doctor before use if you have

- heart disease
- high blood pressure
- thyroid disease
- diabetes
- trouble urinating due to an enlarged prostate gland

When using this product

do not exceed recommended dosage

Stop use and ask a doctor if

- nervousness, dizziness, or sleeplessness occur
- symptoms do not improve within 7 days or occur with a fever

If pregnant or breast-feeding,

ask a health professional before use.

Keep out of reach of children.

In case of overdose, get medical help or contact a Poison Control Center right away (1-800-222-1222).

Directions

adults and children 12 years and over | - take 1 tablet every 12 hours - do not take more than 2 tablets in 24 hours
children under 12 years | do not use this product in children under 12 years of age

Other information

- each tablet contains: calcium 45 mg
- store at 20-25°C (68-77°F) in a dry place
- protect from light
- do not use if blister unit is broken or torn
- see carton end panel for lot number and expiration date
- this product meets the requirements of USP Drug Release Test 3

Inactive ingredients

carnauba wax, colloidal silicon dioxide, dibasic calcium phosphate dihydrate, hypromellose, magnesium stearate, microcrystalline cellulose, polyethylene glycol, polysorbate 80, titanium dioxide

Questions or comments?

1-800-719-9260

Principal Display Panel

Maximum Strength | Non-Drowsy

12-Hour Nasal Decongestant

Pseudoephedrine Hydrochloride Extended-Release Tablets, 120 mg

Nasal Decongestant | Sinus

COMPARE TO SUDAFED® SINUS CONGESTION 12 HOUR MAXIMUM STRENGTH active ingredient

Sinus Pressure + Congestion

10 COATED CAPLETS*

*Capsule-shaped Tablets

Actual Size

100% Money Back Guarantee